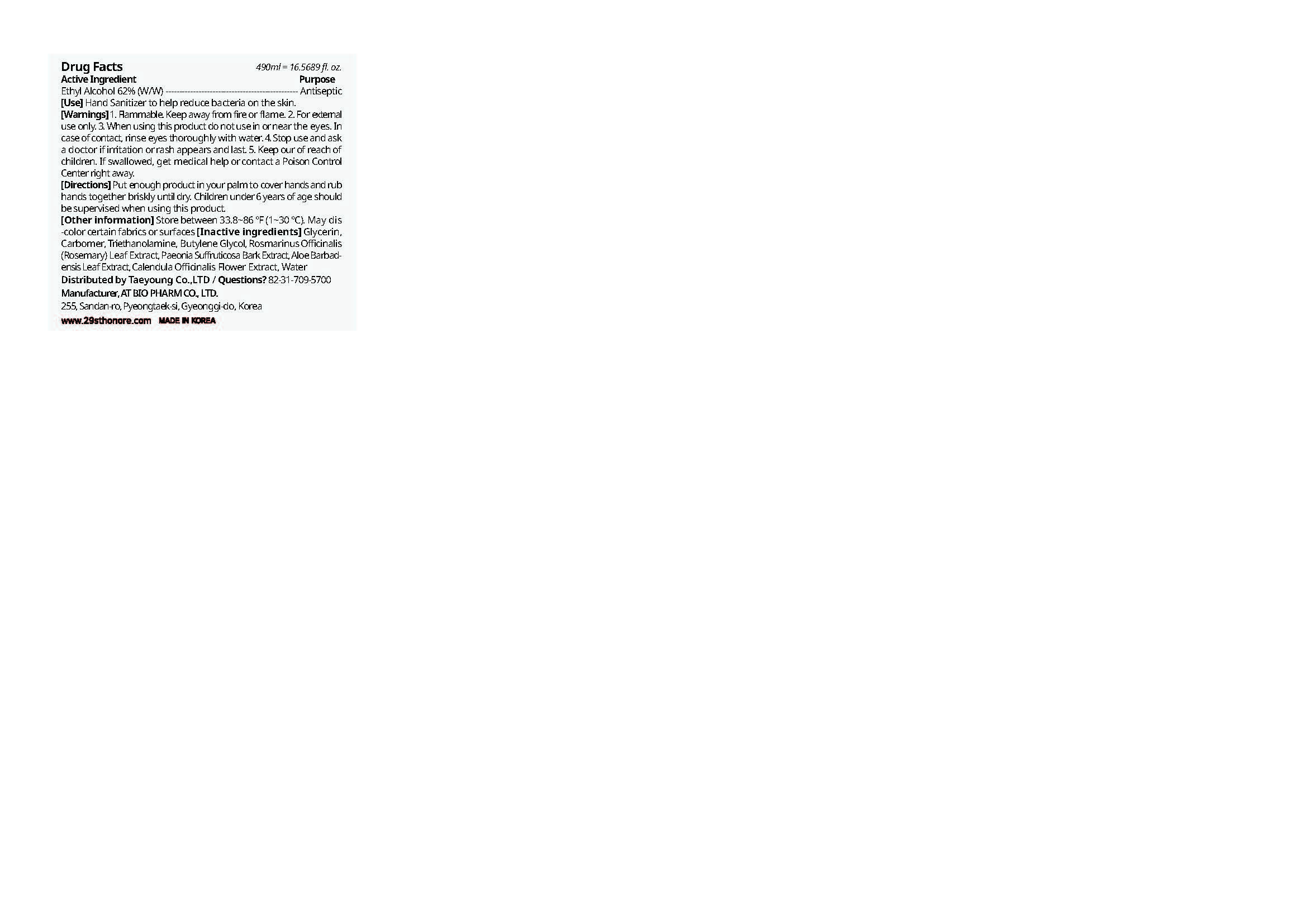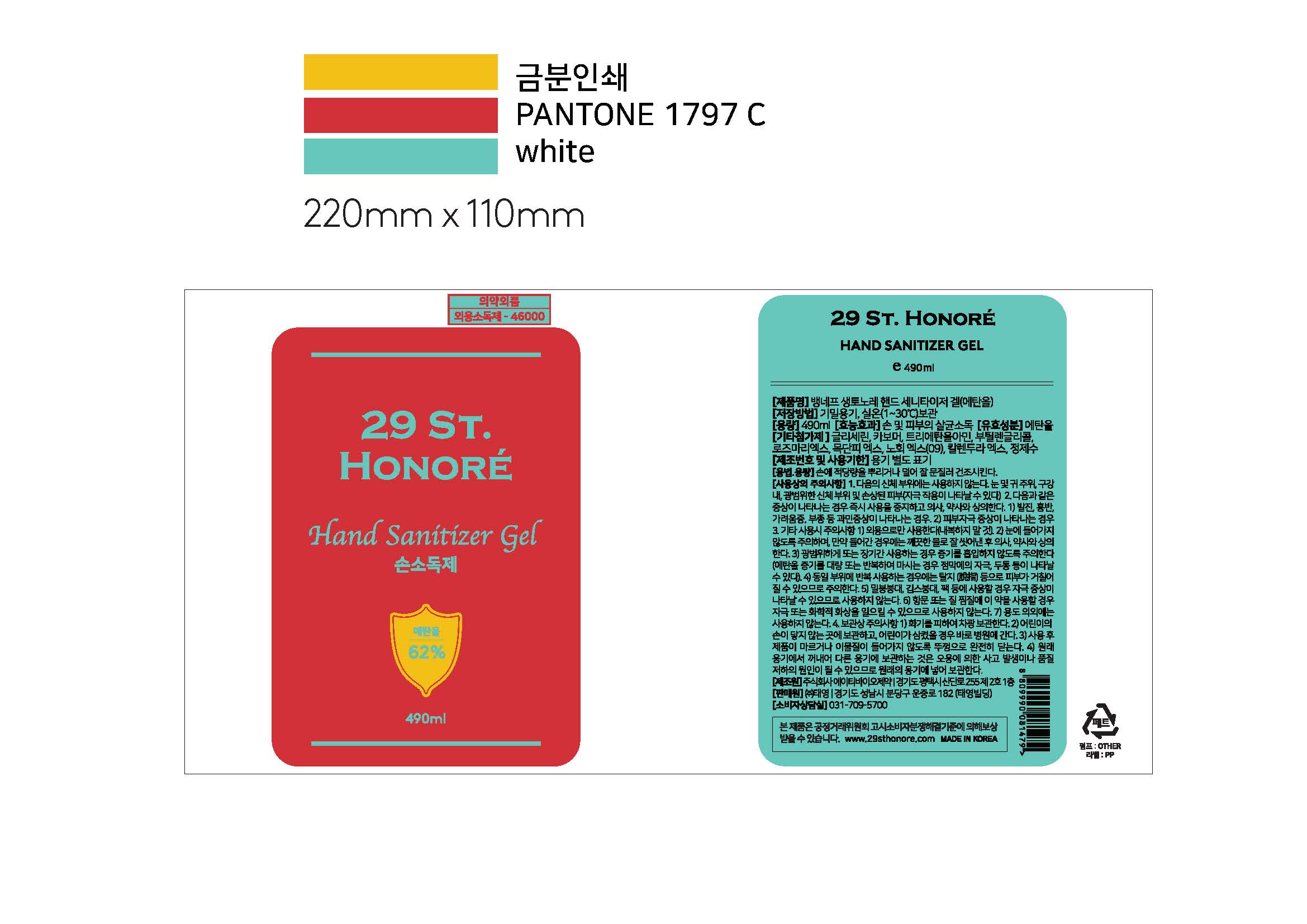 DRUG LABEL: 29 ST. HONORE HAND SANITIZER
NDC: 73932-1000 | Form: GEL
Manufacturer: AT Bio Pharm Co Ltd
Category: otc | Type: HUMAN OTC DRUG LABEL
Date: 20200403

ACTIVE INGREDIENTS: ALCOHOL 62 g/100 mL
INACTIVE INGREDIENTS: GLYCERIN; WATER

Drug Facts

ACTIVE INGREDIENT

Alcohol

INACTIVE INGREDIENT

Glycerin, Carbomer, etc.

PURPOSE

Antiseptic

KEEP OUT OF REACH OF THE CHILDREN

INDICATIONS AND USAGE

For the external use only

WARNINGS

1. Flammable. Keep away from fire or flame. 2. For external
use only. 3. When using this product do not use in or near the eyes. In
case of contact, rinse eyes thoroughly with water. 4. Stop use and ask
a doctor if irritation or rash appears and last. 5. Keep our of reach of
children. If swallowed, get medical help or contact a Poison Control
Center right away.

DOSAGE AND ADMINISTRATION

Put enough product in your palm to cover hands and rub hands together briskly until dry
Children under 6 years of age should be supervised when using this product